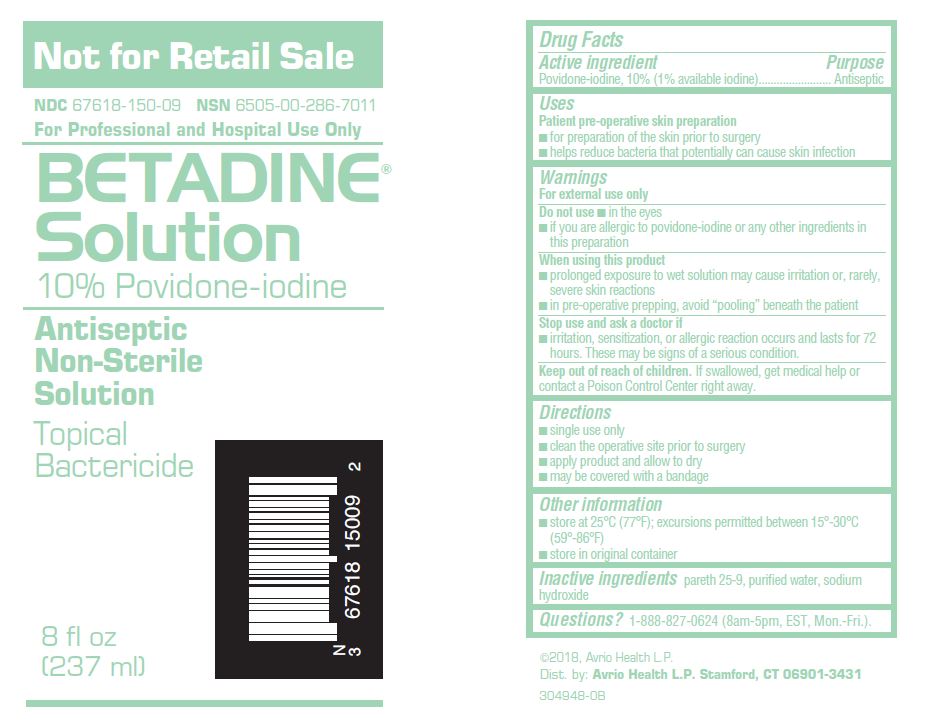 DRUG LABEL: Betadine
NDC: 67618-150 | Form: SOLUTION
Manufacturer: Atlantis Consumer Healthcare, Inc.
Category: otc | Type: HUMAN OTC DRUG LABEL
Date: 20250106

ACTIVE INGREDIENTS: POVIDONE-IODINE 10 mg/1 mL
INACTIVE INGREDIENTS: WATER; SODIUM HYDROXIDE; C12-15 PARETH-9

BETADINE® Solution
10% Povidone-iodine

Drug Facts

Active ingredient

Povidone-iodine, 10%(1% available iodine)

Purpose

Antiseptic

Uses

Patient pre-operative skin preparation

- for preparation of the skin prior to surgery
- helps reduce bacteria that potentially can cause skin infection

Warnings

For external use only

Do not use

- in the eyes
- if you are allergic to povidone-iodine or any other ingredientsin this preparation

When using this product

- single use will reduce the risk of infection from extrinsiccontamination
- prolonged exposure to wet solution may cause irritationor, rarely, severe skin reactions
- in pre-operative prepping, avoid “pooling” beneath the patient

Stop use and ask a doctorif

- irritation, sensitization, or allergic reaction occurs andlasts for 72 hours. These may be signs of a serious condition.

Keep out of reach of children.
If swallowed, get medical help or contact a Poison ControlCenter right away.

Directions

- single use may prevent extrinsic contamination
- clean the operative site prior to surgery
- apply product and allow to dry
- may be covered with a bandage

Other information

- store in original container
- store at 25°C (77°F); excursions permitted between 15°-30°C(59°-86°F)

Inactive ingredients

pareth 25-9, purified water, sodium hydroxide

Dist. by:
Avrio Health L.P.
Stamford, CT 06901-3431

©2018, Avrio Health L.P.

PACKAGE LABEL

BetadineSolution 8 oz
NDC: 67618-150-09